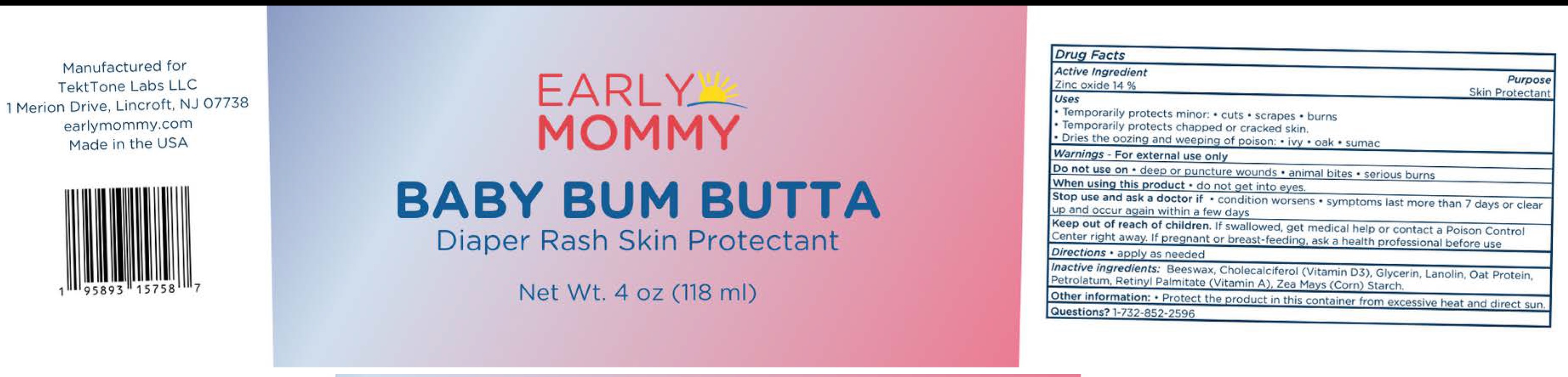 DRUG LABEL: EARLY MOMMY Baby Bum Butta
NDC: 81638-171 | Form: OINTMENT
Manufacturer: TEKT TONE LABS LLC
Category: otc | Type: HUMAN OTC DRUG LABEL
Date: 20250128

ACTIVE INGREDIENTS: ZINC OXIDE 140 mg/1 mL
INACTIVE INGREDIENTS: YELLOW WAX; CHOLECALCIFEROL; GLYCERIN; LANOLIN; PETROLATUM; VITAMIN A PALMITATE; STARCH, CORN

EARLY MOMMY Baby Bum Butta

Active Ingredient

Zinc Oxide 14%

Purpose

Skin protectant

Uses

- Temporarily protects minor:
- cuts
- scrapes
- burns
- Temporarily protects chapped or cracked skin.
- Dries the oozing and weeping of poison:
- ivy
- oak
- sumac

Warnings

For external use only

Do not use on

- deep or puncture wound
- animal bites
- serious burns

When using this product

- do not get into eyes.

Stop use and ask a doctor if

- condition worsens
- symptoms last more than 7 days or clear up and occur again within a few days

Keep out of reach of children.

If swallowed, get medical help or contact a Poison Control Center right away.

If pregnant or breast-feeding,

ask a health professional before use

Directions

- apply as needed

Inactive ingredients:

Beeswax, Cholecalciferol (Vitamin D3), Glycerin, Lanolin, Oat Protein, Petrolatum, Retinyl Palmitate (Vitamin A), Zea Mays (Corn) Starch

Other information:

- Protect the product in this container from excessive heat and direct sun.

Questions?

1-732-852-2596